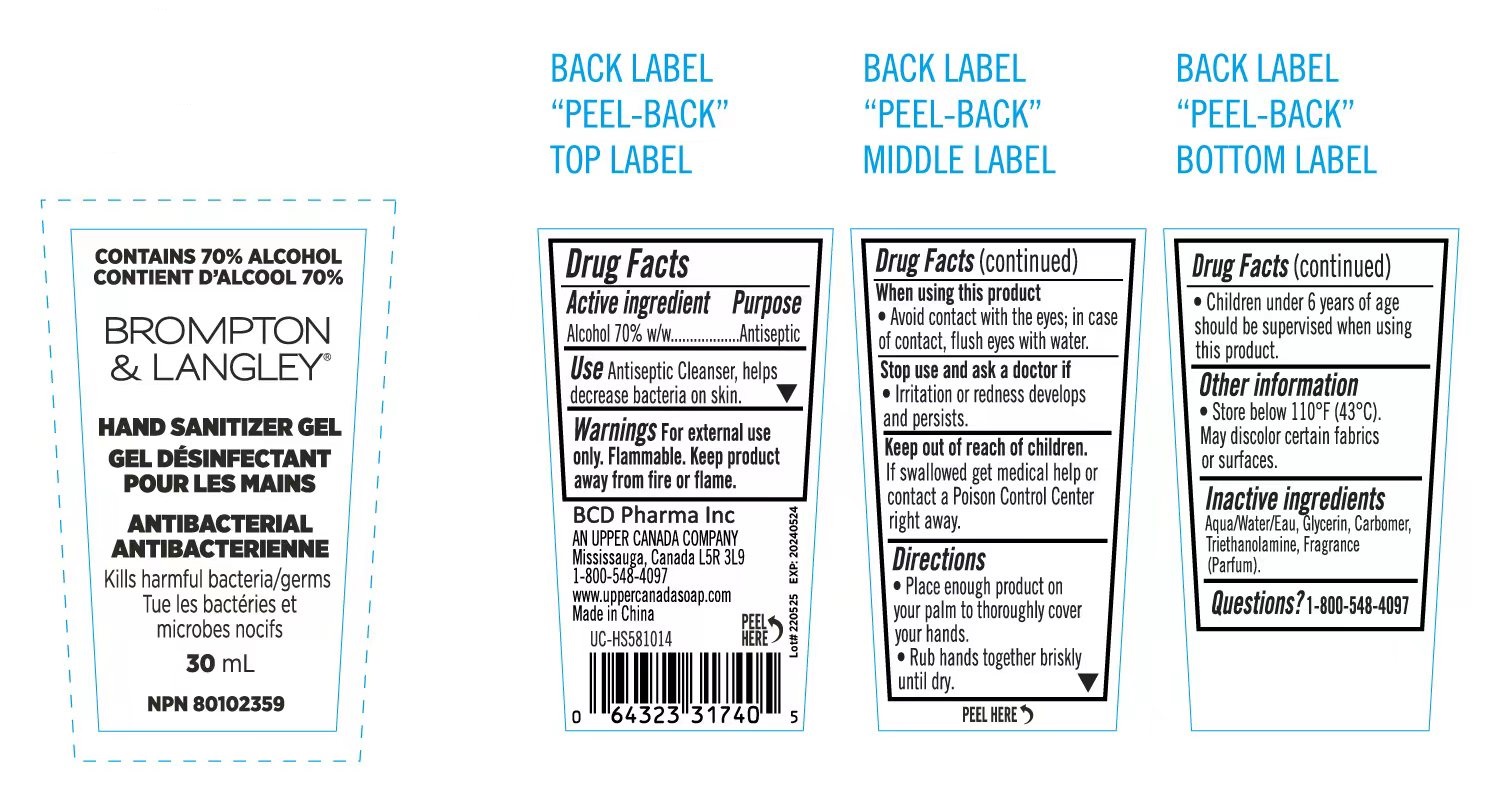 DRUG LABEL: HAND SANITIZER
NDC: 82874-002 | Form: GEL
Manufacturer: Xiamen Tiross Biological Technology Co.,Ltd
Category: otc | Type: HUMAN OTC DRUG LABEL
Date: 20220715

ACTIVE INGREDIENTS: ALCOHOL 70 mL/100 mL
INACTIVE INGREDIENTS: WATER; GLYCERIN; CARBOMER HOMOPOLYMER, UNSPECIFIED TYPE; TROLAMINE

ACTIVE INGREDIENT

Alcohol 70% w/w......................Antiseptic

PURPOSE

Antiseptic Cleanser, helps decrease bacteria on skin.

Keep out of reach of children.If swallowed get medical help or contact a Poison Control Center right away.

INDICATIONS AND USAGE

Antiseptic Cleanser, helps decrease bacteria on skin

Children under 6 years of ageshould be supervised when usingthis product.

WARNINGS

Warnings For external use only. Flammable. Keep product away from fire or flame.

DOSAGE AND ADMINISTRATION

Place enough product onyour palm to thoroughly coveryour hands.
Rub hands together brisklyuntil dry.

STORAGE AND HANDLING

Store below 110°F (43°C).May discolor certain fabricsor surfaces.

INACTIVE INGREDIENT

Aqua/Water/Eau, Glycerin, Carbomer, Triethanolamine, Fragrance(Parfum).